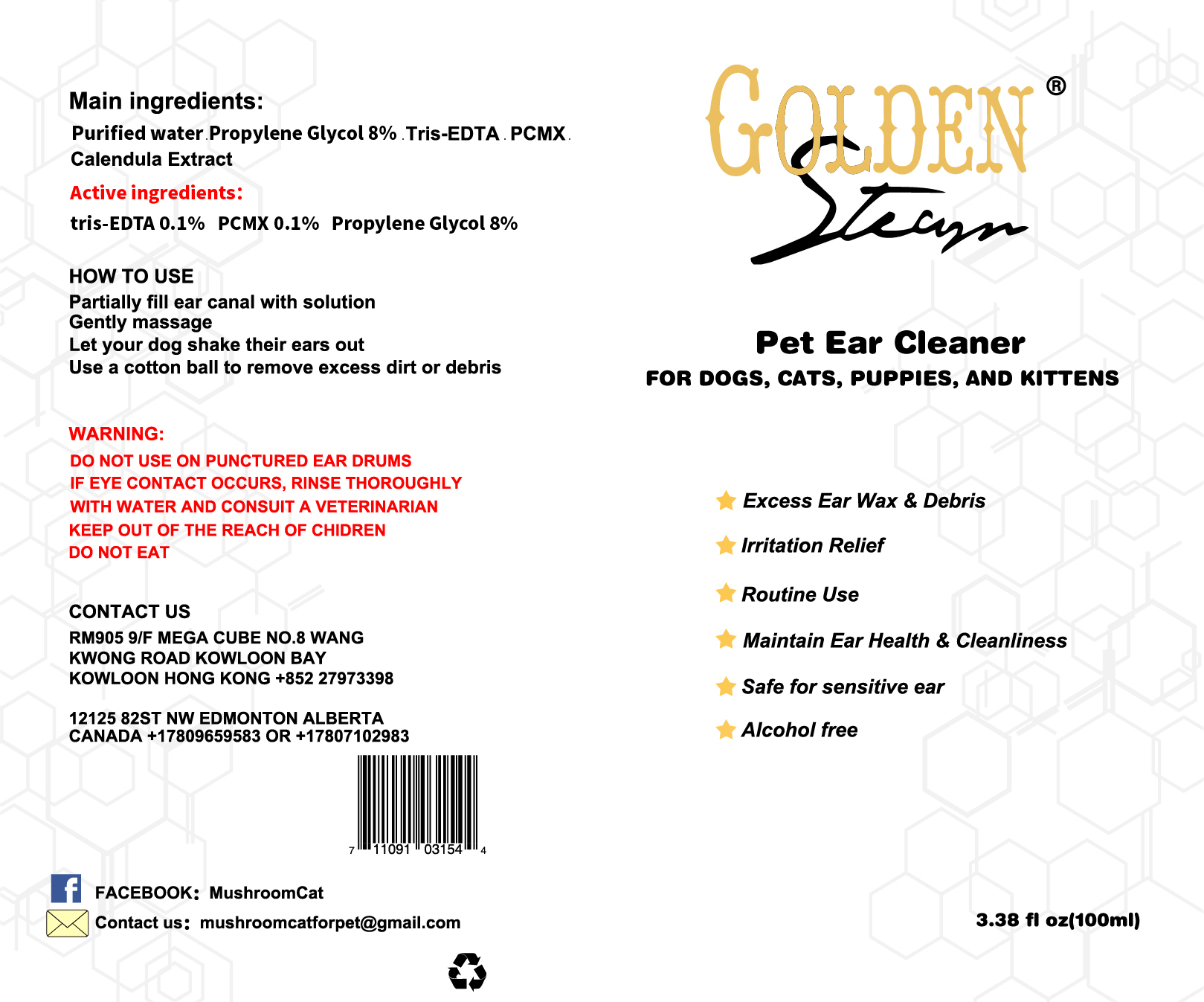 DRUG LABEL: GOLDENSTEAM PET EAR CLEANER
NDC: 40738-002 | Form: LIQUID
Manufacturer: Shenzhen Wan feng Hao Electronic Commerce Co., Ltd.
Category: animal | Type: OTC ANIMAL DRUG LABEL
Date: 20200301

ACTIVE INGREDIENTS: EDETIC ACID 0.001 1/1 1; CHLOROXYLENOL 0.001 1/1 1; PROPYLENE GLYCOL 0.08 1/1 1
INACTIVE INGREDIENTS: WATER; CALENDULADIOL

DO NOT USE ON PUNCTURED EAR DRUMS
IF EYE CONTACT OCCURS, RINSE THOROUGHLY
WITH WATER AND CONSUIT A VETERINARIAN
KEEP OUT OFTHE R EACH OF CHIDREN
DO NOT EAT